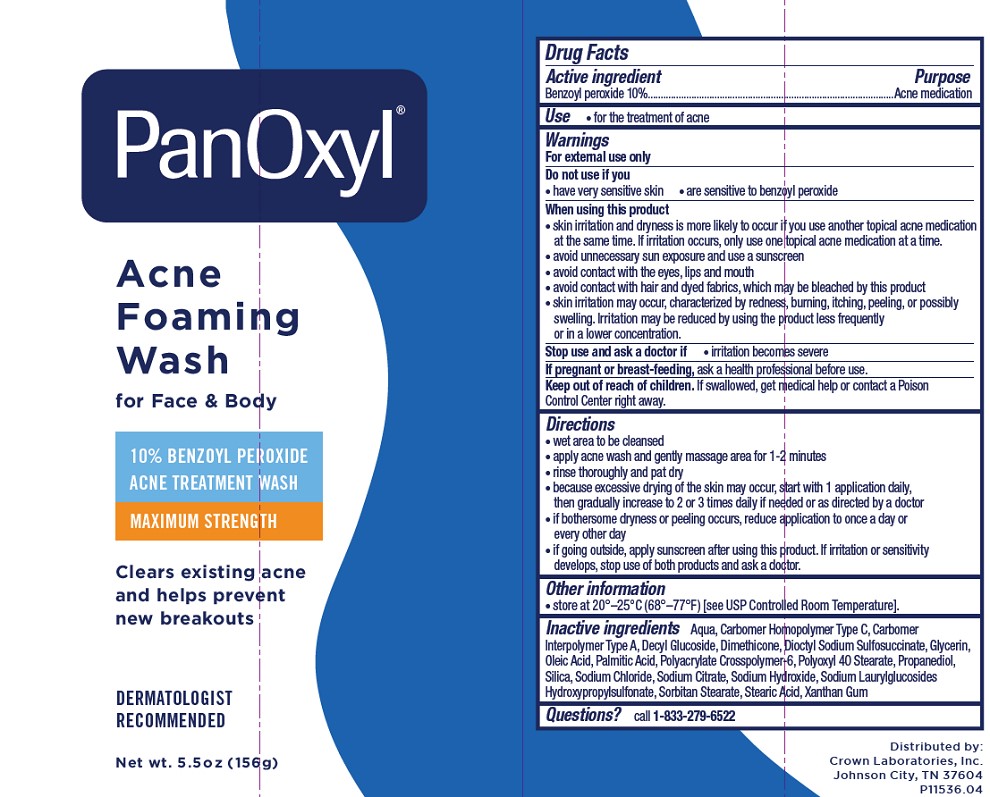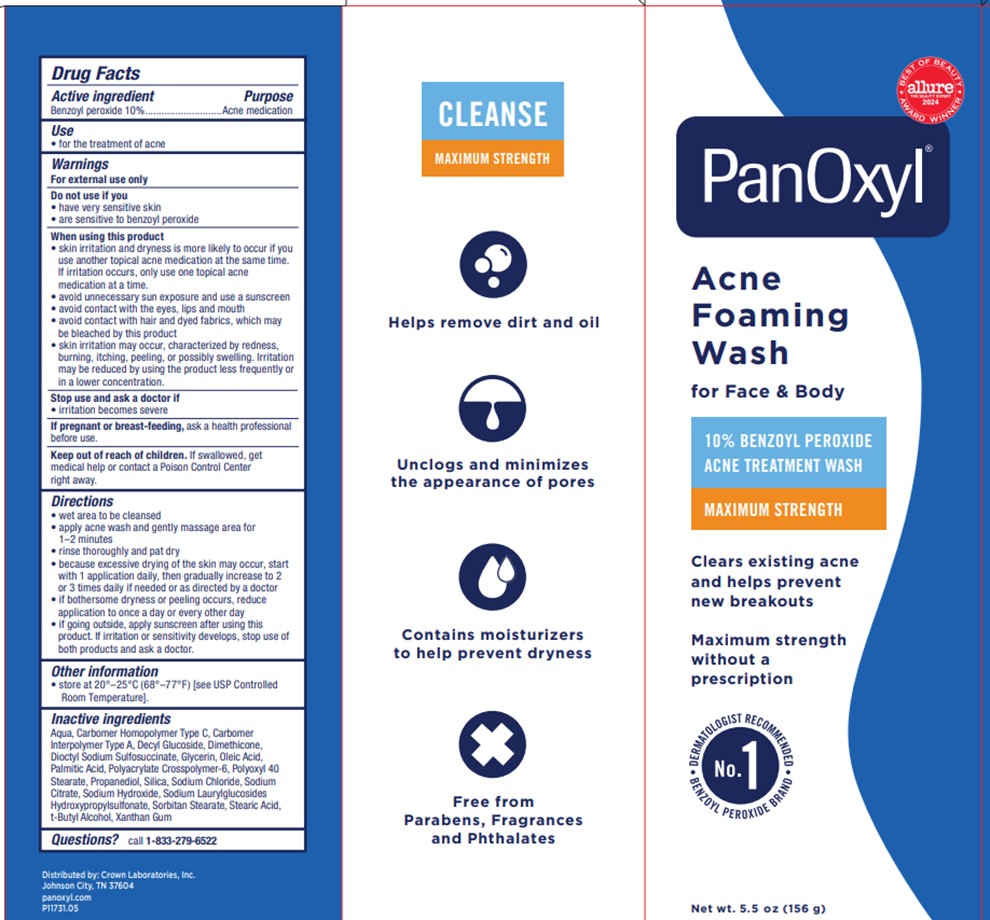 DRUG LABEL: PanOxyl
NDC: 0316-0228 | Form: CREAM
Manufacturer: Crown Laboratories
Category: otc | Type: HUMAN OTC DRUG LABEL
Date: 20260112

ACTIVE INGREDIENTS: BENZOYL PEROXIDE 100 mg/1 g
INACTIVE INGREDIENTS: XANTHAN GUM; CARBOMER INTERPOLYMER TYPE A (ALLYL SUCROSE CROSSLINKED); DIMETHICONE; DOCUSATE SODIUM; PALMITIC ACID; SODIUM CITRATE; SODIUM CHLORIDE; SORBITAN MONOSTEARATE; SILICON DIOXIDE; AMMONIUM ACRYLOYLDIMETHYLTAURATE, DIMETHYLACRYLAMIDE, LAURYL METHACRYLATE AND LAURETH-4 METHACRYLATE COPOLYMER, TRIMETHYLOLPROPANE TRIACRYLATE CROSSLINKED (45000 MPA.S); WATER; GLYCERIN; DECYL GLUCOSIDE; STEARIC ACID; CARBOMER HOMOPOLYMER TYPE C (ALLYL PENTAERYTHRITOL CROSSLINKED); SODIUM HYDROXIDE; POLYOXYL 40 STEARATE; PROPANEDIOL; SODIUM LAURYLGLUCOSIDES HYDROXYPROPYLSULFONATE; TERT-BUTYL ALCOHOL

Panoxyl Acne Foaming Wash

Active ingredient

Benzoyl peroxide 10%

Purpose

Acne medication

Use

- for the treatment of acne

Warnings

For external use only

Do not use if you

- have very sensitive skin
- are sensitive to benzoyl peroxide

When using this product

- skin irritation and dryness is more likely to occur if you use another topical acne medication at the same time. If irritation occurs, only use one topical acne medication at a time.
- avoid unnecessary sun exposure and use a sunscreen
- avoid contact with the eyes, lips and mouth
- avoid contact with hair and dyed fabrics, which may be bleached by this product
- skin irritation may occur, characterized by redness, burning, itching, peeling, or possibly swelling. Irritation may be reduced by using the product less frequently or in a lower concentration.

Stop use and ask a doctor if

- irritation becomes severe

If pregnant or breast-feeding,

ask a health professional before use.

Keep out of reach of children.

If swallowed, get medical help or contact a Poison Control Center right away.

Directions

- wet area to be cleansed
- apply acne wash and gently massage area for 1-2 minutes
- rinse thoroughly and pat dry
- because excessive drying of the skin may occur, start with 1 application daily, then gradually increase to 2 or 3 times daily if needed or as directed by a doctor
- if bothersome dryness or peeling occurs, reduce application to once a day or every other day
- if going outside, apply sunscreen after using this product. If irritation or sensitivity develops, stop use of both products and ask a doctor.

Other information

- Store at 20o - 25oC (68o - 77oF) [see USP Controlled Room Temperature].

Inactive ingredients

carbomer homopolymer type C, carbomer interpolymer type A, decyl glucoside, dimethicone, dioctyl sodium sulfosuccinate, glycerin, palmitic acid, polyacrylate crosspolymer-6, polyoxyl 40 stearate, propanediol, purified water, silica, sodium chloride, sodium citrate, sodium hydroxide, sodium laurylglucosides hydroxypropylsulfonate, sorbitan stearate, sorbitol, stearic acid, t-butyl alcohol, xanthan gum

Questions or comments?

call 1-833-279-6522

Panoxyl 10% Tube

PanOxyl®

ACNE FOAMING WASH

for Face & Body

10% Benzoyl Peroxide

Acne Treatment Wash

Maximum Strength

Clears existing acne and helps prevent new breakouts

Net wt. 5.5oz (156g)

DERMATOLOGIST RECOMMENDED

Distributed by: Crown Laboratories, Inc. Johnson City, TN 37604

P11536.04

Panoxyl 10% Carton

PanOxyl®

ACNE FOAMING WASH

for Face & Body

10% Benzoyl Peroxide

Acne Treatment Wash

Maximum Strength

Clears existing acne and helps prevent new breakouts

Maximum strength without a prescription

No.1 DERMATOLOGIST RECOMMENDED BENZOYL PEROXIDE BRAND

Net wt. 5.5oz (156g)

P11731.05